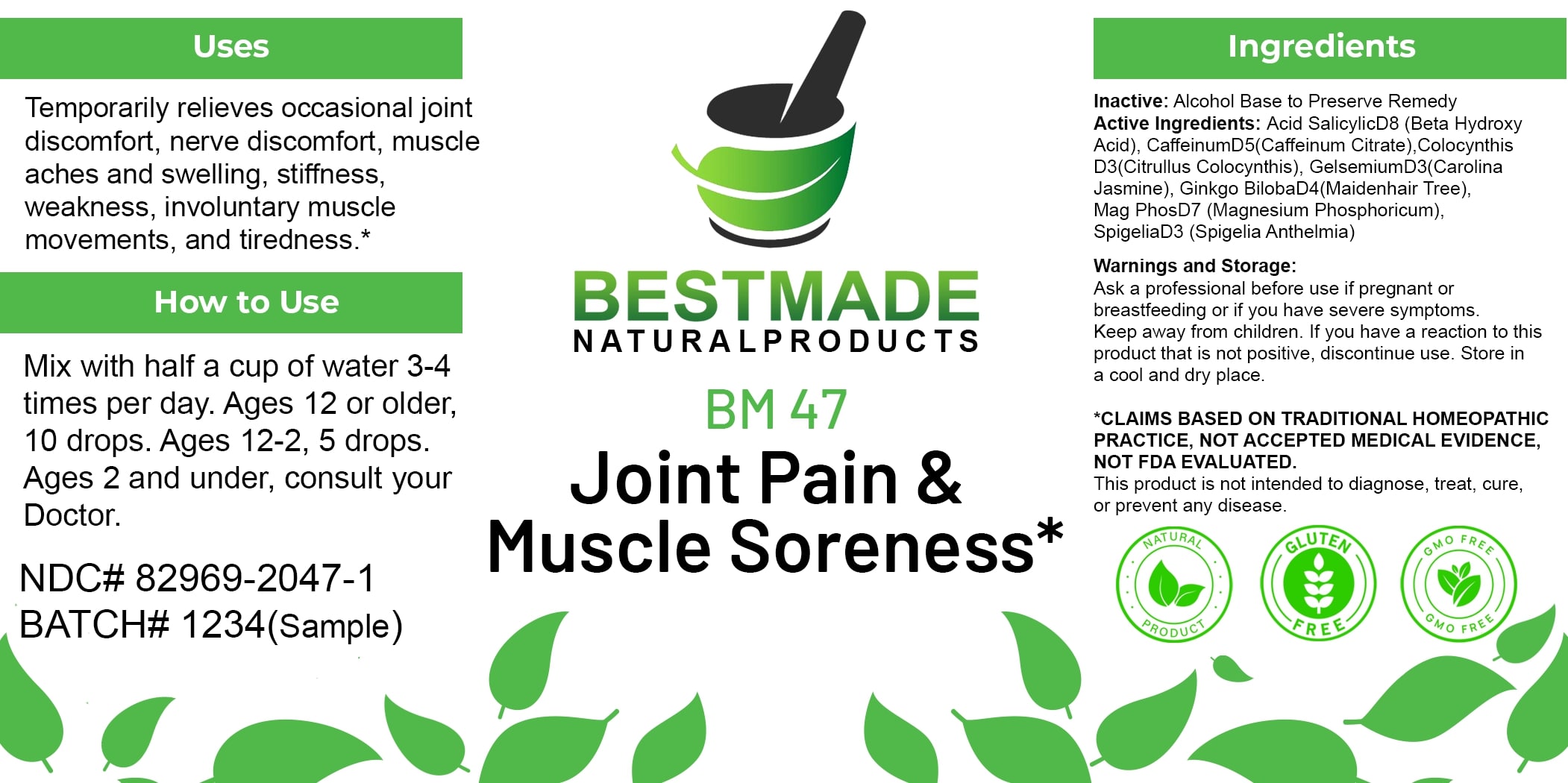 DRUG LABEL: Bestmade Natural Products BM47
NDC: 82969-2047 | Form: LIQUID
Manufacturer: Bestmade Natural Products
Category: homeopathic | Type: HUMAN OTC DRUG LABEL
Date: 20250123

ACTIVE INGREDIENTS: GINKGO 30 [hp_C]/30 [hp_C]; GELSEMIUM SEMPERVIRENS ROOT 30 [hp_C]/30 [hp_C]; MAGNESIUM PHOSPHATE, DIBASIC TRIHYDRATE 30 [hp_C]/30 [hp_C]; CITRULLUS COLOCYNTHIS FRUIT PULP 30 [hp_C]/30 [hp_C]; CAFFEINE 30 [hp_C]/30 [hp_C]; SALICYLIC ACID 30 [hp_C]/30 [hp_C]; SPIGELIA ANTHELMIA 30 [hp_C]/30 [hp_C]
INACTIVE INGREDIENTS: ALCOHOL 30 [hp_C]/30 [hp_C]

BM47

DOSAGE AND ADMINISTRATION

How to Use

Mix with half a cup of water 3-4 times per day. Ages 12 or older, 10 drops. Ages 12-2, 5 drops. Ages 2 and under, consult your Doctor.

INACTIVE INGREDIENT

Ingredients

Inactive: Alcohol Base to Preserve Remedy

ACTIVE INGREDIENT

Active Ingredients: Acid Salicylic D8 (Beta Hydroxy Acid), Caffeinum D5 (Caffeinum Citrate), Colocynthis D3 (Citrullus Colocynthis), Gelsemium D3 (Carolina Jasmine), Ginkgo Biloba D4 (Maidenhair Tree), Mag Phos D7 (Magnesium Phosphoricum), Spigelia D3 (Spigelia Anthelmia)

Uses

Temporarily relieves occasional joint discomfort, nerve discomfort, muscle aches and swelling, stiffness, weakness, involuntary muscle movements, and tiredness.*

*CLAIMS BASED ON TRADITIONAL HOMEOPATHIC PRACTICE, NOT ACCEPTED MEDICAL EVIDENCE, NOT FDA EVALUATED.

This product is not intended to diagnose, treat, cure, or prevent any disease.

Uses

Temporarily relieves occasional joint discomfort, nerve discomfort, muscle aches and swelling, stiffness, weakness, involuntary muscle movements, and tiredness.*

*CLAIMS BASED ON TRADITIONAL HOMEOPATHIC PRACTICE, NOT ACCEPTED MEDICAL EVIDENCE, NOT FDA EVALUATED.

This product is not intended to diagnose, treat, cure, or prevent any disease.

KEEP OUT OF REACH OF CHILDREN

Warnings and Storage:

Ask a professional before use if pregnant or breastfeeding or if you have severe symptoms. Keep away from children. If you have a reaction to this product that is not positive, discontinue use. Store in a cool and dry place.

Warnings and Storage:

Ask a professional before use if pregnant or breastfeeding or if you have severe symptoms. Keep away from children. If you have a reaction to this product that is not positive, discontinue use. Store in a cool and dry place.

*CLAIMS BASED ON TRADITIONAL HOMEOPATHIC PRACTICE, NOT ACCEPTED MEDICAL EVIDENCE, NOT FDA EVALUATED.

This product is not intended to diagnose, treat, cure, or prevent any disease.

Entire package label